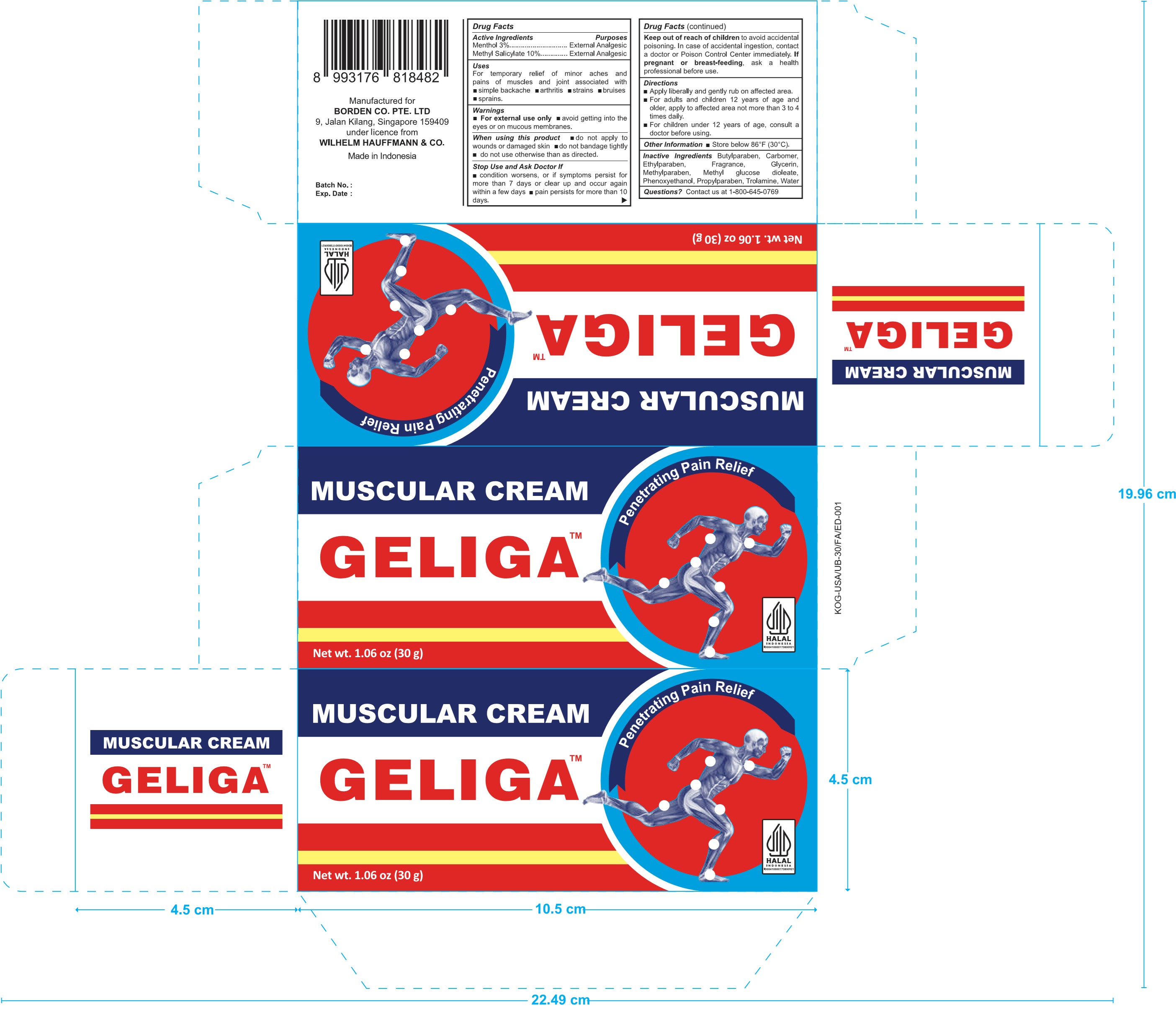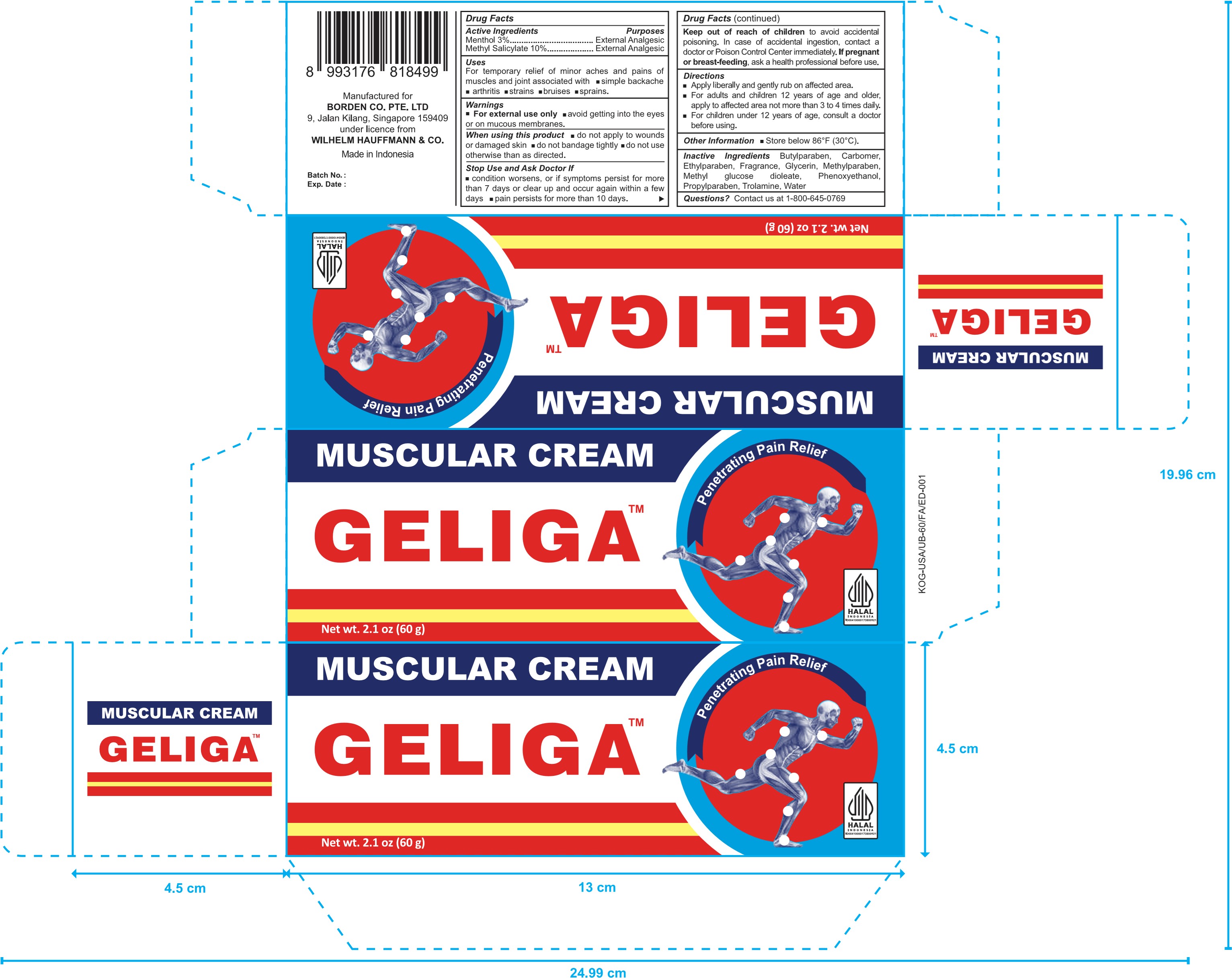 DRUG LABEL: Geliga
NDC: 60954-004 | Form: CREAM
Manufacturer: PT. EAGLE INDO PHARMA
Category: otc | Type: HUMAN OTC DRUG LABEL
Date: 20241002

ACTIVE INGREDIENTS: MENTHOL 3 g/100 g; METHYL SALICYLATE 10 g/100 g
INACTIVE INGREDIENTS: METHYLPARABEN; WATER; METHYL GLUCOSE DIOLEATE; PROPYLPARABEN; PHENOXYETHANOL; TROLAMINE; ETHYLPARABEN; GLYCERIN; BUTYLPARABEN; CARBOMER HOMOPOLYMER, UNSPECIFIED TYPE

Geliga Muscular Cream

Active Ingredients

- Menthol 3%
- Methyl Salicylate 10%

Purpose

External Analgeisc

Uses

For temporary relief of minor aches and pains of muscles and joints associated with simple backaches, arthritis, strains, bruises, and sprains.

Warnings

For external use only.

Avoid contact with the eyes or mucous membrane.

When using this product

- Do not apply to wounds or damaged skin.
- Do not bandage tightly.
- Do not use otherwise than as directed.

Stop use and ask doctor if

- Condition worsens.
- Symptoms persist for more than 7 days or clear up and occur again within a few days.
- Pain persists for more than 10 days.

Pregnancy or breast-feeding

If pregnant or breast-feeding, ask a health professional before use.

Keep out of reach of children to avoid accidental poisoning. In case of accidental ingestion, contact a doctor or Poison Control Center immediately.

Directions

- Apply liberally and rub gently onto affected area.
- Adults and children of 12 years of age and older, apply not more than 3 to 4 times daily.
- Children under 12 years of age, consult a doctor before using.

Other information

Store below 86oF (30oC).

Inactive Ingredients

Butylparaben, Carbomer, Ethylparaben, Fragrance, Glycerin, Methylparaben, Methyl glucose dioelate, Phenoxyethanol, Propylparaben, Trolamine, Water

Questions

Contact us at 1-800-645-0769

Package Label

30g NDC: 60954-004-30

Package Label

60g NDC: 60954-004-60